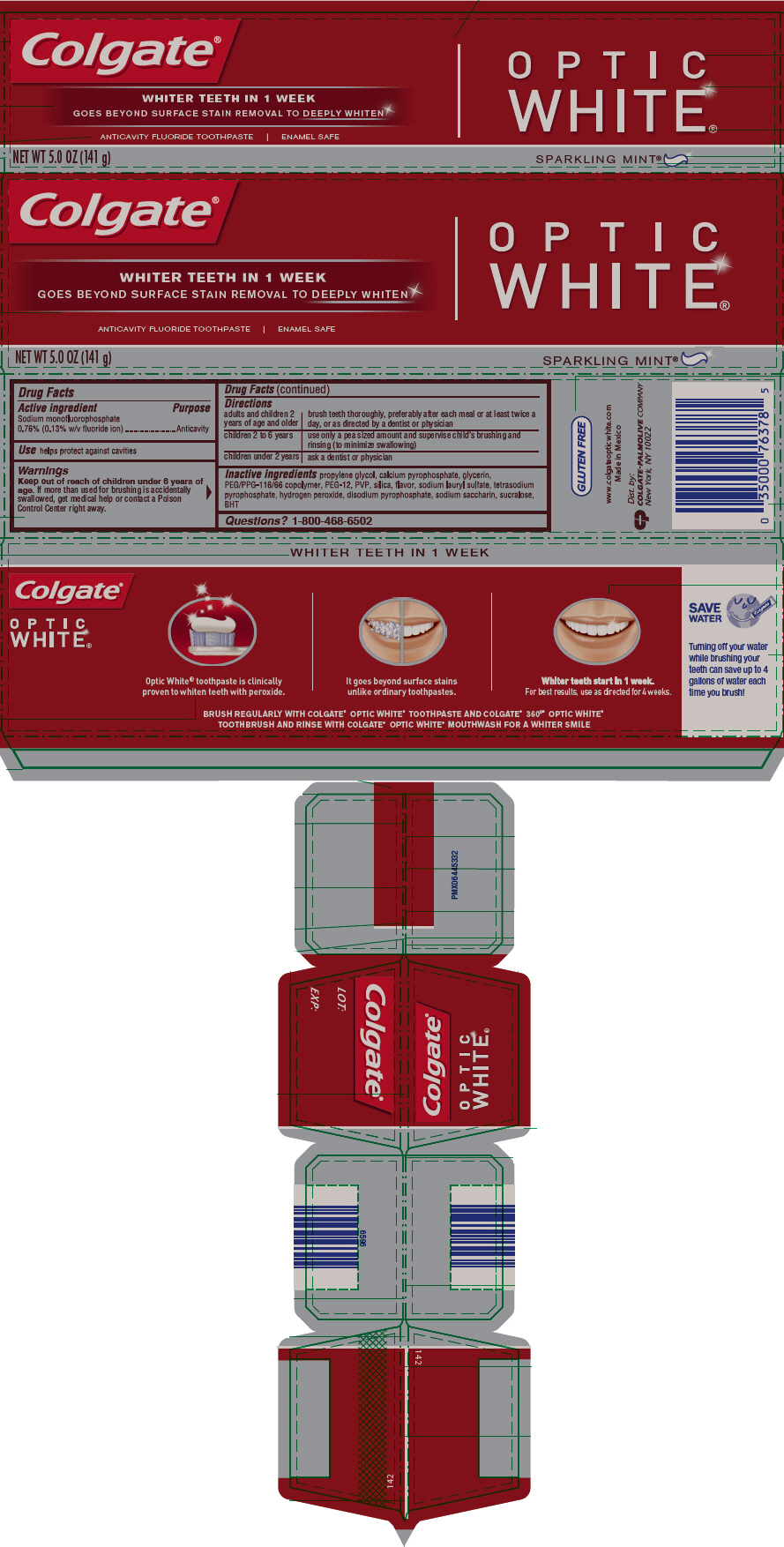 DRUG LABEL: Colgate Optic White Sparkling Mint Flavor
NDC: 67659-330 | Form: PASTE, DENTIFRICE
Manufacturer: Team Technologies, Inc
Category: otc | Type: HUMAN OTC DRUG LABEL
Date: 20160520

ACTIVE INGREDIENTS: SODIUM MONOFLUOROPHOSPHATE 1 mg/1 g
INACTIVE INGREDIENTS: PROPYLENE GLYCOL 341.6 mg/1 g; CALCIUM PYROPHOSPHATE; GLYCERIN; PEG/PPG-116/66 COPOLYMER; POLYETHYLENE GLYCOL 600; POVIDONE K15; SILICON DIOXIDE; SODIUM LAURYL SULFATE; SODIUM PYROPHOSPHATE; HYDROGEN PEROXIDE; SODIUM ACID PYROPHOSPHATE; SACCHARIN SODIUM; SUCRALOSE; BUTYLATED HYDROXYTOLUENE

Colgate® Optic White® Sparkling Mint® Flavor Toothpaste

Drug Facts

Active ingredient

Sodium monofluorophosphate 0.76% (0.13% w/v fluoride ion)

Purpose

Anticavity

Use

helps protect against cavities

Warnings

Keep out of reach of children under 6 years of age. If more than used for brushing is accidentally swallowed, get medical help or contact a Poison Control Center right away.

Directions

adults and children 2 years of age and older | brush teeth thoroughly, preferably after each meal or at least twice a day, or as directed by a dentist or physician
children 2 to 6 years | use only a pea sized amount and supervise child's brushing and rinsing (to minimize swallowing)
children under 2 years | ask a dentist or physician

Inactive ingredients

propylene glycol, calcium pyrophosphate, glycerin, PEG/PPG-116/66 copolymer, PEG-12, PVP, silica, flavor, sodium lauryl sulfate, tetrasodium pyrophosphate, hydrogen peroxide, disodium pyrophosphate, sodium saccharin, sucralose, BHT

Questions?

1-800-468-6502

Dist. by:
COLGATE-PALMOLIVE COMPANY
New York, NY 10022

PRINCIPAL DISPLAY PANEL - 141 g Tube Carton

Colgate®

WHITER TEETH IN 1 WEEK
GOES BEYOND SURFACE STAIN REMOVAL TO DEEPLY WHITEN

ANTICAVITY FLUORIDE TOOTHPASTE | ENAMEL SAFE

OPTIC
WHITE ®

NET WT 5.0 OZ (141 g)

SPARKLING MINT®